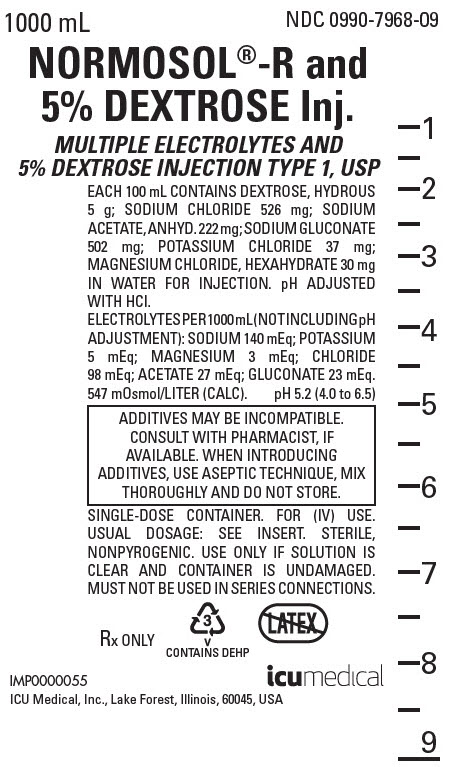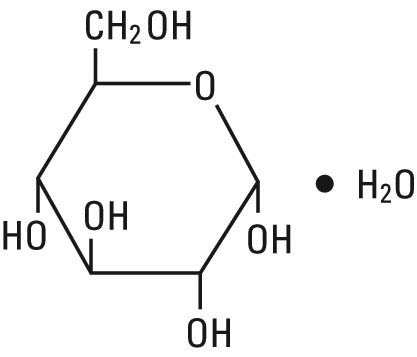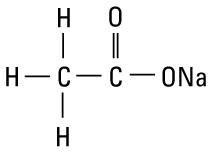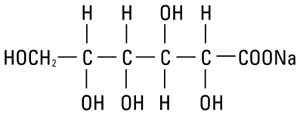 DRUG LABEL: Normosol-R and Dextrose
NDC: 0990-7968 | Form: INJECTION, SOLUTION
Manufacturer: ICU Medical Inc.
Category: prescription | Type: HUMAN PRESCRIPTION DRUG LABEL
Date: 20251029

ACTIVE INGREDIENTS: DEXTROSE MONOHYDRATE 5 g/100 mL; SODIUM CHLORIDE 526 mg/100 mL; SODIUM ACETATE ANHYDROUS 222 mg/100 mL; SODIUM GLUCONATE 502 mg/100 mL; POTASSIUM CHLORIDE 37 mg/100 mL; MAGNESIUM CHLORIDE 30 mg/100 mL
INACTIVE INGREDIENTS: WATER; HYDROCHLORIC ACID

Normosol®-R and 5% Dextrose Injection

MULTIPLE ELECTROLYTES AND 5% DEXTROSE INJECTION TYPE 1, USP

For Replacing Acute Losses of Extracellular Fluid

Flexible Plastic Container

Rx only

DESCRIPTION

Normosol-R and 5% Dextrose Injection is a sterile, nonpyrogenic solution of balanced electrolytes (with dextrose) in water for injection. The solution is administered by intravenous infusion for parenteral replacement of acute losses of extracellular fluid (with minimal carbohydrate calories).

Each 100 mL of Normosol-R and 5% Dextrose Injection contains dextrose 5 g; sodium chloride 526 mg; sodium acetate, anhydrous 222 mg; sodium gluconate 502 mg; potassium chloride 37 mg; magnesium chloride, hexahydrate 30 mg; pH adjusted with hydrochloric acid.

See TABLE for summary of electrolyte content, caloric value and characteristics of this solution.

The solution contains no bacteriostat, antimicrobial agent or added buffer (except for pH adjustment) and is intended only for use as a single-dose injection. When smaller doses are required the unused portion should be discarded.

Normosol-R and 5% Dextrose Injection is a parenteral fluid, electrolyte and nutrient replenisher.

Dextrose, USP is chemically designated D-glucose monohydrate (C6H12O6 • H20), a hexose sugar freely soluble in water. It has the following structural formula:

Sodium Chloride, USP is chemically designated NaCl, a white crystalline powder freely soluble in water.

Potassium Chloride, USP is chemically designated KCl, a white granular powder freely soluble in water.

Magnesium Chloride, USP is chemically designated magnesium chloride hexahydrate (MgCl2 • 6H2O) deliquescent crystals very soluble in water.

Sodium Acetate, USP, is chemically designated sodium acetate anhydrous (C2H3NaO2), a hygroscopic powder soluble in water. It has the following structural formula:

Sodium gluconate is chemically designated C6H11NaO7, the normal sodium salt of gluconic acid soluble in water. It has the following structural formula:

Water for Injection, USP is chemically designated H20.

The flexible plastic container is fabricated from a specially formulated polyvinylchloride. Water can permeate from inside the container into the overwrap but not in amounts sufficient to affect the solution significantly. Solutions in contact with the plastic container may leach out certain chemical components from the plastic in very small amounts; however, biological testing was supportive of the safety of the plastic container materials. Exposure to temperatures above 25°C/77°F during transport and storage will lead to minor losses in moisture content. Higher temperatures lead to greater losses. It is unlikely that these minor losses will lead to clinically significant changes within the expiration period.

CLINICAL PHARMACOLOGY

When administered intravenously, Normosol-R and 5% Dextrose Injection provides water and electrolytes with carbohydrate calories for replacement of acute extracellular fluid losses without disturbing normal electrolyte relationships. The electrolyte composition approaches that of the principal ions of normal plasma (extracellular fluid). The electrolyte concentration is approximately isotonic in relation to the extracellular fluid (approx. 280 mOsmol/liter) and provides a physiologic sodium to chloride ratio, normal plasma concentrations of potassium and magnesium and two bicarbonate alternates, acetate and gluconate. Dextrose provides minimal calories and renders the solution hypertonic.

Solutions containing carbohydrate in the form of dextrose restore blood glucose levels and supply calories. Carbohydrate in the form of dextrose may aid in minimizing liver glycogen depletion and exerts a protein-sparing action. Dextrose injected parenterally undergoes oxidation to carbon dioxide and water.

Sodium chloride in water dissociates to provide sodium (Na^+) and chloride (Cl‾) ions. Sodium (Na^+) is the principal cation of the extracellular fluid and plays a large part in the therapy of fluid and electrolyte disturbances. Chloride (Cl‾) has an integral role in buffering action when oxygen and carbon dioxide exchange occurs in the red blood cells. The distribution and excretion of sodium (Na^+) and chloride (Cl‾) are largely under the control of the kidney which maintains a balance between intake and output.

Potassium chloride in water dissociates to provide potassium (K^+) and chloride (Cl‾) ions. Potassium is the chief cation of body cells (160 mEq/liter of intracellular water). It is found in low concentration in plasma and extracellular fluids (3.5 to 5.0 mEq/liter in a healthy adult and child over 10 days old; 3.5 to 6.0 mEq/liter in a child less than 10 days old). Potassium plays an important role in electrolyte balance.

Normally about 80 to 90% of the potassium intake is excreted in the urine; the remainder in the stools and to a small extent, in the perspiration. The kidney does not conserve potassium well so that during fasting or in patients on a potassium-free diet, potassium loss from the body continues resulting in potassium depletion.

Magnesium chloride in water dissociates to provide magnesium (Mg^++) and chloride (Cl‾) ions. Magnesium is the second most plentiful cation of the intracellular fluids. It is an important cofactor for enzymatic reactions and plays an important role in neurochemical transmission and muscular excitability. Normal plasma concentration ranges from 1.5 to 2.5 or 3.0 mEq per liter. Magnesium is excreted solely by the kidney at a rate proportional to the plasma concentration and glomerular filtration.

Sodium acetate provides sodium (Na^+) and acetate (CH3COO‾) ions, the latter anion (a source of hydrogen ion acceptors) serving as an alternate source of bicarbonate (HCO3‾) by metabolic conversion in the liver. This has been shown to proceed readily even in the presence of severe liver disease. Thus, acetate anion exerts a mild systemic antiacidotic action that may be advantageous during fluid and electrolyte replacement therapy.

Sodium gluconate provides sodium (Na^+) and gluconate (C6H1107‾) ions. Although gluconate is a theoretical alternate metabolic source of bicarbonate (HC03‾) anion, a significant antiacidotic action has not been established. Thus, the gluconate anion serves primarily to complete the cation-anion balance of the solution.

Water is an essential constituent of all body tissues and accounts for approximately 70% of total body weight. Average normal adult daily requirement ranges from two to three liters (1.0 to 1.5 liters each for insensible water loss by perspiration and urine production).

Average normal pediatric daily requirements are based on the child’s weight as described in the table below:

Weight | Fluid Requirements
Up to 10 kg | 100 mL/kg
11 to 20 kg | 1,000 mL + 50 mL/kg for each
 | kg above 10 kg
Above 20 kg | 1,500 mL + 20 mL/kg for each
 | kg above 20 kg

Water balance is maintained by various regulatory mechanisms. Water distribution depends primarily on the concentration of electrolytes in the body compartments and sodium (Na^+) plays a major role in maintaining physiologic equilibrium.

INDICATIONS AND USAGE

Normosol-R and 5% Dextrose Injection is indicated for replacement of acute extracellular fluid volume losses in surgery, trauma, burns or shock. Normosol-R and 5% Dextrose also can be used as an adjunct to restore a decrease in circulatory volume in patients with moderate blood loss. The solution is not intended to supplant transfusion of whole blood or packed red cells in the presence of uncontrolled hemorrhage or severe reductions of red cell volume.

CONTRAINDICATIONS

None known.

WARNINGS

Solutions containing sodium ions should be used with great care, if at all, in patients with congestive heart failure, severe renal insufficiency and in clinical states in which there exists edema with sodium retention.

Solutions which contain potassium should be used with great care, if at all, in patients with hyperkalemia, severe renal failure and in conditions in which potassium retention is present.

In patients with diminished renal function, administration of solutions containing sodium or potassium ions may result in sodium or potassium retention. Because elderly patients are more likely to have decreased renal function, care should be taken in dose selection, and it may be useful to monitor renal function during fluid replacement with Normosol-R and 5% Dextrose.

Solutions containing acetate or gluconate ions should be used with great care in patients with metabolic or respiratory alkalosis. Acetate or gluconate should be administered with great care in those conditions in which there is an increased level or an impaired utilization of these ions, such as severe hepatic insufficiency.

The intravenous administration of this solution can cause fluid and/or solute overloading resulting in dilution of serum electrolyte concentrations, overhydration, congested states or pulmonary edema.

Elderly patients may be at increased risk for the development of fluid overloading and dilutional hyponatremia following Normosol-R and 5% Dextrose administration.

The risk of dilutional states is inversely proportional to the electrolyte concentrations of administered parenteral solutions. The risk of solute overload causing congested states with peripheral and pulmonary edema is directly proportional to the electrolyte concentrations of such solutions.

PRECAUTIONS

Normosol-R and 5% Dextrose Injection should be used with caution in severe renal impairment because of the danger of hyperkalemia. As with all intravenous solutions, care should be taken to avoid circulatory overload, especially in patients with cardiac or pulmonary disorders. Normosol-R and 5% Dextrose is not intended to correct acidosis or large deficits of individual electrolytes, nor to replace blood or plasma expanders when these are indicated.

Clinical evaluation and periodic laboratory determinations are necessary to monitor changes in fluid balance, electrolyte concentrations and acid-base balance during prolonged parenteral therapy or whenever the condition of the patient warrants such evaluation.

Caution must be exercised in the administration of parenteral fluids, especially those containing sodium ions, to patients receiving corticosteroids or corticotropin.

Solutions containing acetate or gluconate ions should be used with caution, as excess administration may result in metabolic alkalosis.

Solutions containing dextrose should be used with caution in patients with known subclinical or overt diabetes mellitus.

Do not administer unless solution is clear and container is undamaged. Discard unused portion.

Pregnancy Category C

Animal reproduction studies have not been conducted with Normosol-R and 5% Dextrose Injection. It is also not known whether this solution can cause fetal harm when administered to a pregnant woman or can affect reproduction capacity. This solution should be given to a pregnant woman only if clearly needed.

Pediatric Use

The safety and effectiveness in the pediatric population are based on the similarity of the clinical conditions of the pediatric and adult populations. In neonates or very small infants the volume of fluid may affect fluid and electrolyte balance.

Frequent monitoring of serum glucose concentrations is required when dextrose is prescribed to pediatric patients, particularly neonates and low birth weight infants.

In very low birth weight infants, excessive or rapid administration of dextrose injection may result in increased serum osmolality and possible intracerebral hemorrhage.

Geriatric Use

Clinical studies of Normosol-R and 5% Dextrose did not include sufficient numbers of subjects aged 65 and over to determine whether they respond differently from younger subjects. Other reported clinical experience has not identified differences in response between elderly and younger patients. In general, dose selection for an elderly patient should be cautious, usually starting at the low end of the dosing range, reflecting the greater frequency of decreased hepatic, renal, or cardiac function, and of concomitant disease or other drug therapy.

Elderly patients have been shown to secrete higher levels of antidiuretic hormone than younger patients, which may increase the risk of fluid overloading, and dilutional hyponatremia in these patients. (See WARNINGS.)

This drug is known to be substantially excreted by the kidney, and the risk of toxic reactions to this drug may be greater in patients with impaired renal function. Because elderly patients are more likely to have decreased renal function, care should be taken in dose selection, and it may be useful to monitor renal function. (See WARNINGS.)

ADVERSE REACTIONS

Reactions which may occur because of the solution or the technique of administration include febrile response, infection at the site of injection, venous thrombosis or phlebitis extending from the site of injection, extravasation and hypervolemia.

If an adverse reaction does occur, discontinue the infusion, evaluate the patient, institute appropriate therapeutic countermeasures and save the remainder of the fluid for examination if deemed necessary.

OVERDOSAGE

In the event of overhydration or solute overload, re-evaluate the patient and institute appropriate corrective measures. (See WARNINGS, PRECAUTIONS and ADVERSE REACTIONS.)

DOSAGE AND ADMINISTRATION

Normosol-R and 5% Dextrose Injection is administered by intravenous infusion. The amount to be infused is based on replacement of losses of extracellular fluid volume in the individual patient. Up to 3 times the volume of estimated blood loss during and after surgery can be given to correct circulatory volume when there is only a moderate loss of blood.

As reported in the literature, the dosage and constant infusion rate of intravenous dextrose must be selected with caution in pediatric patients, particularly neonates and low birth weight infants, because of the increased risk of hyperglycemia/hypoglycemia.

Drug Interactions

Additives may be incompatible. Consult with pharmacist, if available. When introducing additives, use aseptic technique, mix thoroughly and do not store.

Normosol-R and 5% Dextrose solution does not contain calcium to avoid precipitation of calcium salts that may occur when certain drugs are added.

Parenteral drug products should be inspected visually for particulate matter or discoloration prior to administration, whenever solution and container permit. (See PRECAUTIONS.)

INSTRUCTIONS FOR USE

To Open:

Tear outer wrap at notch and remove solution container. Some opacity of the plastic due to moisture absorption during the sterilization process may be observed. This is normal and does not affect the solution quality or safety. If supplemental medication is desired, follow directions below before preparing for administration.

To Add Medication

1. Prepare additive port.
2. Using aseptic technique and an additive delivery needle of appropriate length, puncture resealable additive port at target area, inner diaphragm and inject. Withdraw needle after injecting medication.
3. The additive port may be protected by covering with an additive cap.
4. Mix container contents thoroughly.

To Administer

1. Attach administration set per manufacturer’s instructions.
2. Regulate rate of administration per institutional policy.

WARNING: Do not use flexible container in series connections.

HOW SUPPLIED

Normosol-R and 5% Dextrose Injection (Multiple Electrolytes and 5% Dextrose Injection Type 1, USP) is supplied in a 1000 mL single-dose flexible plastic container (NDC No. 0409–7968–09 and 0990-7968-09).

ICU Medical is transitioning NDC codes from the "0409" to a "0990" labeler code. Both NDC codes are expected to be in the market for a period of time.

TABLE
Electrolyte Content, Caloric Value and Characteristics
 | Milliequivalents per Liter
 |  |  |  | HC0^-3 (alternates) |  |  | Cal* | mOsmol/L | Tonicity
 | Na^+ | K^+ | Mg^++ | Cl^- | Acetate | Gluconate | per Liter | (calc.) | (total contents) | pH
Normosol-R and; 5% Dextrose | 140 | 5 | 3 | 98** | 27 | 23 | 185 | 547 | Hypertonic | 5.2; (4.0 to 6.5)

* Normosol-R and 5% Dextrose calories derived from dextrose (170) and gluconate (15).

**Not including hydrochloric acid.

Store at 20 to 25°C (68 to 77°F). [See USP Controlled Room Temperature.] Protect from freezing.

®Normosol − multiple electrolyte solution, ICU Medical, Inc.

Revised: March, 2020

IFU0000172

ICU Medical, Inc., Lake Forest, Illinois, 60045, USA

PRINCIPAL DISPLAY PANEL - 1000 mL Bag Label

1000 mL
NDC 0990-7968-09

NORMOSOL®-R and
5% DEXTROSE Inj.

MULTIPLE ELECTROLYTES AND
5% DEXTROSE INJECTION TYPE 1, USP

EACH 100 mL CONTAINS DEXTROSE, HYDROUS
5 g; SODIUM CHLORIDE 526 mg; SODIUM
ACETATE, ANHYD. 222 mg; SODIUM GLUCONATE
502 mg; POTASSIUM CHLORIDE 37 mg;
MAGNESIUM CHLORIDE, HEXAHYDRATE 30 mg
IN WATER FOR INJECTION. pH ADJUSTED
WITH HCl.

ELECTROLYTES PER 1000 mL (NOT INCLUDING pH
ADJUSTMENT): SODIUM 140 mEq; POTASSIUM
5 mEq; MAGNESIUM 3 mEq; CHLORIDE
98 mEq; ACETATE 27 mEq; GLUCONATE 23 mEq.
547 mOsmol/LITER (CALC).
pH 5.2 (4.0 to 6.5)

ADDITIVES MAY BE INCOMPATIBLE.
CONSULT WITH PHARMACIST, IF
AVAILABLE. WHEN INTRODUCING
ADDITIVES, USE ASEPTIC TECHNIQUE, MIX
THOROUGHLY AND DO NOT STORE.

SINGLE-DOSE CONTAINER. FOR (IV) USE.
USUAL DOSAGE: SEE INSERT. STERILE,
NONPYROGENIC. USE ONLY IF SOLUTION IS
CLEAR AND CONTAINER IS UNDAMAGED.
MUST NOT BE USED IN SERIES CONNECTIONS.

Rx ONLY

3
v
CONTAINS DEHP

IMP0000055

icumedical

ICU Medical, Inc., Lake Forest, Illinois, 60045, USA